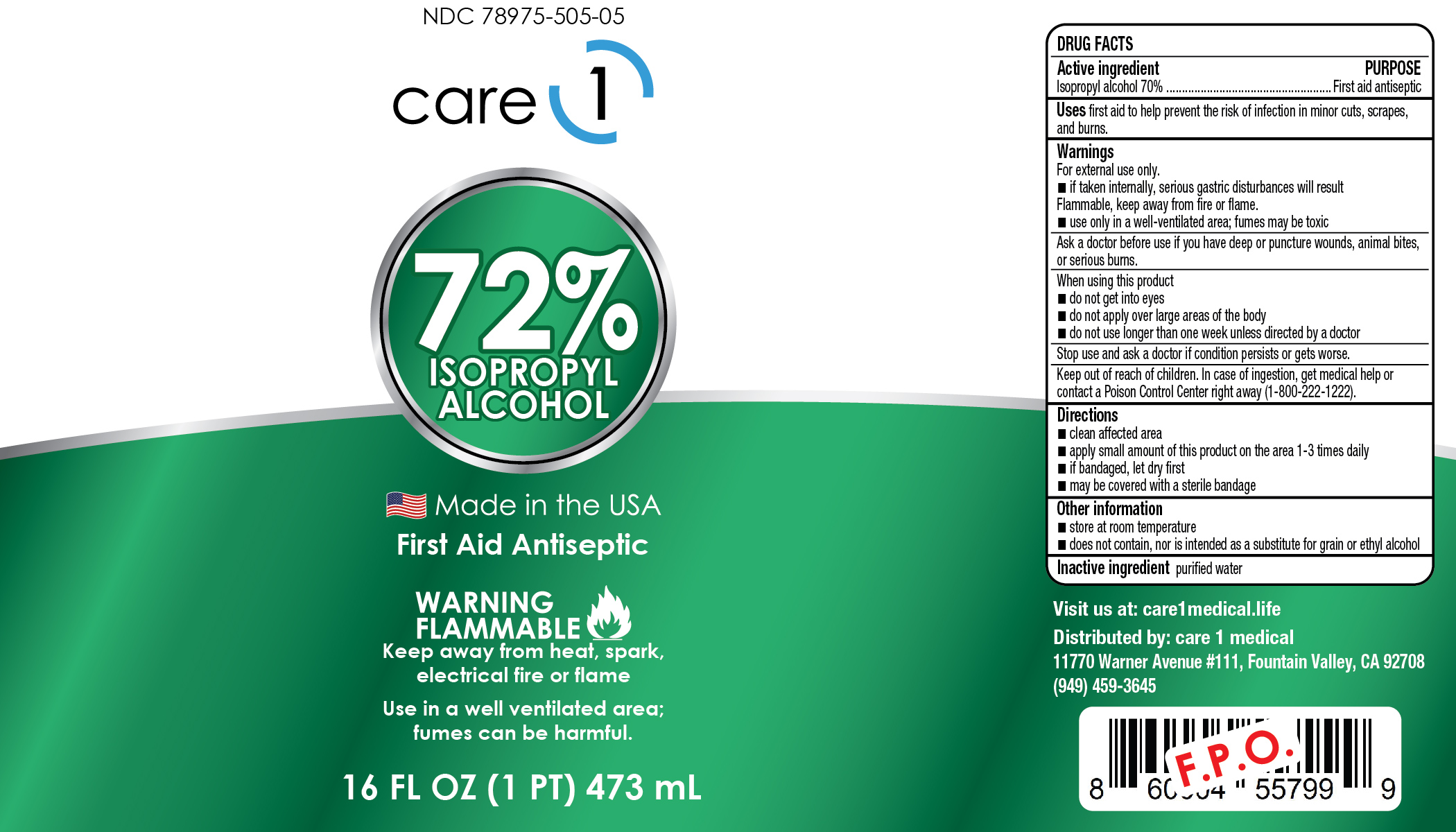 DRUG LABEL: Care1 Isopropyl Rubbing Alcohol 72%
NDC: 78975-505 | Form: LIQUID
Manufacturer: Lauree LLC
Category: otc | Type: HUMAN OTC DRUG LABEL
Date: 20201001

ACTIVE INGREDIENTS: ISOPROPYL ALCOHOL 72 mL/100 mL
INACTIVE INGREDIENTS: WATER

Care1 ISOPROPYL RUBBING ALCOHOL 72%- isopropyl alcohol liquid

This is a hand sanitizer manufactured according to the Temporary Policy for Preparation of Certain Alcohol-Based Hand Sanitizer Products During the Public Health Emergency (CoViD-19); Guidance for Industry.

The hand sanitizer is manufactured using only the following United States Pharmacopoeia (USP) grade ingredients in the preparation of the product (percentage in final product formulation) consistent with World Health Organization (WHO) recommendations:

1. Isopropyl Alcohol (75%, v/v) in an aqueous solution denatured according to Alcohol and Tobacco Tax and Trade Bureau regulations in 27 CFR part 20.
2. Glycerol (1.45% v/v).
3. Hydrogen peroxide (0.125% v/v).
4. Sterile distilled water or boiled cold water.

The firm does not add other active or inactive ingredients. Different or additional ingredients may impact the quality and potency of the product.

Active Ingredient(s)

Isopropyl Alcohol 72% v/v. Purpose: Antiseptic

Purpose

First aid antiseptic

Use

Helps prevent the risk of infection in minor cuts, scrapes and burns.

Warnings

For external use only. Flammable. Keep away from heat or flame

Ask a doctor before use

for deep wounds, animal bites or serious burns

WHEN USING

•do not get into eyes

• do not apply over large area of the body

• do not use longer than 1 week

Stop use and ask a doctor if irritation or rash occurs. These may be signs of a serious condition.

Keep out of reach of children. If swallowed, get medical help or contact a Poison Control Center right away.

Directions

• clean the affected area

• apply 1 to 3 times daily

Other information

• does not contain, nor is intended as a substitute for grain or ethyl alcohol

• will produce serious gastric disturbances if taken internally

Inactive ingredients

Purified water USP

Package Label - Principal Display Panel

473 ml NDC: 78975-505-05